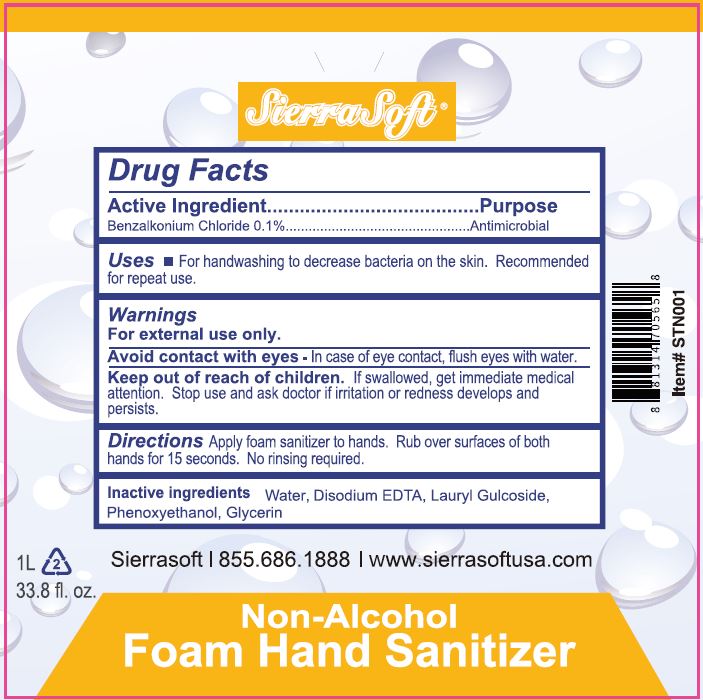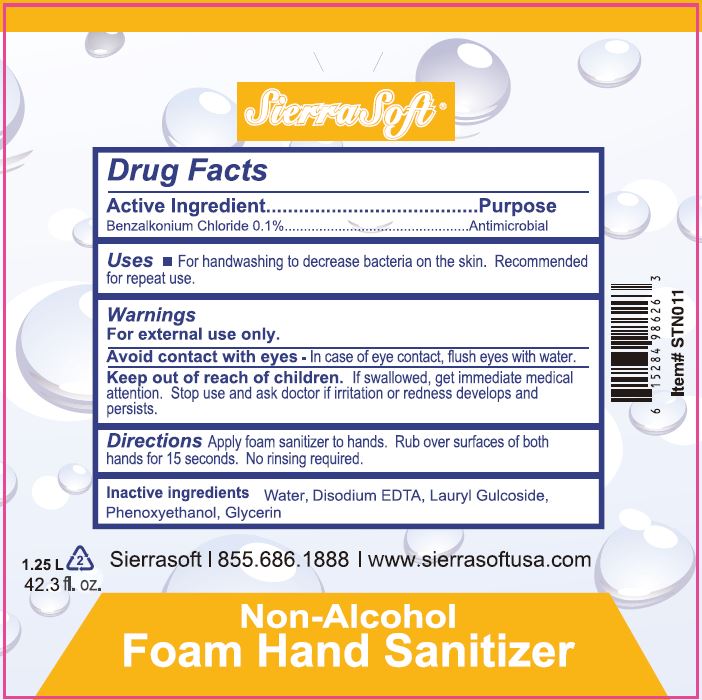 DRUG LABEL: Sierra Soft Non-Alcohol Foam Sanitizer
NDC: 70415-103 | Form: GEL
Manufacturer: CWGC LA Inc.
Category: otc | Type: HUMAN OTC DRUG LABEL
Date: 20230921

ACTIVE INGREDIENTS: BENZALKONIUM CHLORIDE 0.1 g/100 mL
INACTIVE INGREDIENTS: WATER; EDETATE DISODIUM; LAURYL GLUCOSIDE; PHENOXYETHANOL; GLYCERIN

CWGC (as PLD) - SIERRA SOFT NON-ALCOHOL FOAM HAND SANITIZER (70415-103)

Active ingredient

BENZALKONIUM CHLORIDE 0.13%

Purpose

Antibacterial

Uses

- For sanitizing to reduce bacteria on the skin.

Warnings

For external use only

Keep out of reach of children. If swallowed, get medical help or contact a Poison Control Center right away.

Directions

TO USE, SIMPLY PLACE CARTRIDGE INTO DISPENSER AND USE STRAIGHT; DO NOT DILUTE. APPLY 1 PUMP OF SANITIZER ONTO HANDS AND RUB INTO SKIN. NO RINSING REQUIRED.

Inactive ingredients

Water, Propylene Glycol, Cocamidopropyl Betaine, Cocamine Oxide, Disodium EDTA, DMDM Hydantoin, Triethanolamine, Fragrance, FD&C Yellow No.5, FD&C Blue No.1.